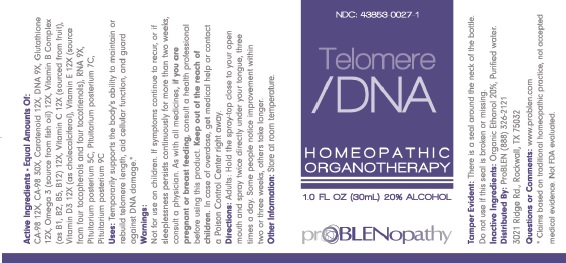 DRUG LABEL: Telomere - DNA
NDC: 43853-0027 | Form: SPRAY
Manufacturer: ProBLEN
Category: homeopathic | Type: HUMAN OTC DRUG LABEL
Date: 20221130

ACTIVE INGREDIENTS: CYCLOASTRAGENOL 12 [hp_X]/30 mL; BETA CAROTENE 12 [hp_X]/30 mL; HERRING SPERM DNA 9 [hp_X]/30 mL; GLUTATHIONE 12 [hp_X]/30 mL; OMEGA-3 FATTY ACIDS 12 [hp_X]/30 mL; SUS SCROFA PITUITARY GLAND, POSTERIOR 5 [hp_C]/30 mL; SACCHAROMYCES CEREVISIAE RNA 9 [hp_X]/30 mL; THIAMINE 12 [hp_X]/30 mL; RIBOFLAVIN 12 [hp_X]/30 mL; PANTOTHENIC ACID 12 [hp_X]/30 mL; CYANOCOBALAMIN 12 [hp_X]/30 mL; ASCORBIC ACID 12 [hp_X]/30 mL; CHOLECALCIFEROL 12 [hp_X]/30 mL; .ALPHA.-TOCOPHEROL 12 [hp_X]/30 mL
INACTIVE INGREDIENTS: ALCOHOL; WATER

Telomere - DNA

Active Ingredients - Equal Amounts Of:

CA-98 12X, CA-98 30X, Carotenoid 12X, DNA 9X, Glutathione 12X, Omega 3 (source from fish oil) 12X, Vitamin B Complex (as B1, B2, B5, B12) 12X, Vitamin C 12X (sourced from fruit), Vitamin D3 12X (as cholecalciferol), Vitamin E 12X (source from four tocopherols and four tocotrienols), RNA 9X, Pituitarium posterium 5C, Pituitarium posterium 7C, Pituitarium posterium 9C.

*Claims based on traditional homeopathic practice, not accepted medical evidence. Not FDA evaluated.

INDICATIONS AND USAGE

Uses: Temporarily supports the body's ability to maintain or rebuild telomere length, aid cellular function and guard against DNA damage.*

WARNINGS

Warnings: Not for use on children. If symptoms continue to recur, or if sleeplessness persists continuously for more than two weeks, consult a physician. I nsomnia may be a symptom of a serious underlying medical illness. As with all medicines, if you are pregnant or breast feeding, consult a health professional before using this product. Keep out of reach of children. In case of overdose, get medical help or contact a Poison Control Center right away.

Keep out of reach of children.

DOSAGE AND ADMINISTRATION

Directions: Adults: Hold the spray-top close to your open mouth and spray twice directly under your tongue, three times a day. Some people notice improvement within three weeks, others take longer.

Other Information: Store at room temperature.

Inactive Ingredients: Organic Ethanol 20%, Purified water.

QUESTIONS

Distributed By: ProBLEN (888) 326-2121

3021 Ridge Rd., Rockwall, TX 75032

PACKAGE LABEL

PURPOSE

NDC: 43853-0027-1

Telomere / DNA

HOMEOPATHIC

ORGANOTHERAPY

PURPOSE

Temporarily supports the body's ability to maintain or rebuild telomere length, aid cellular function, and gaurd against DNA damage.*